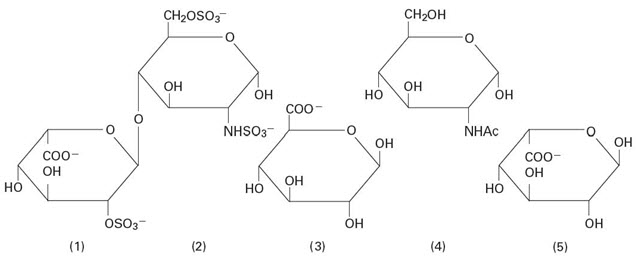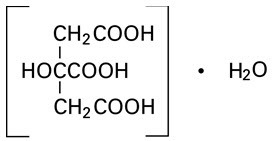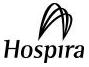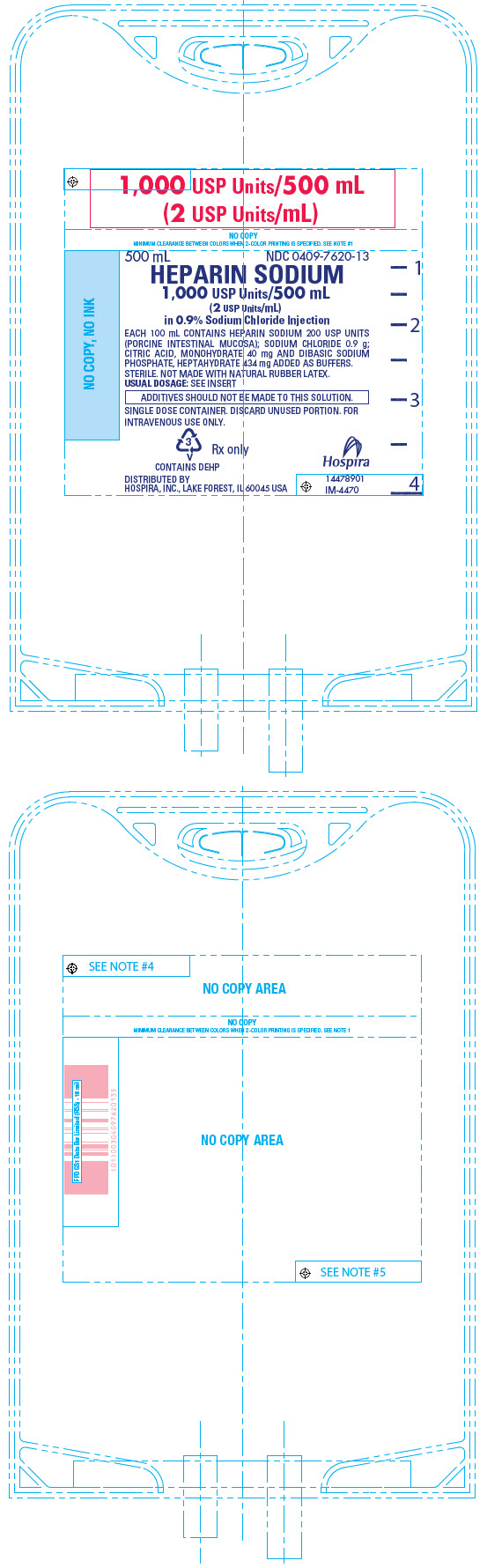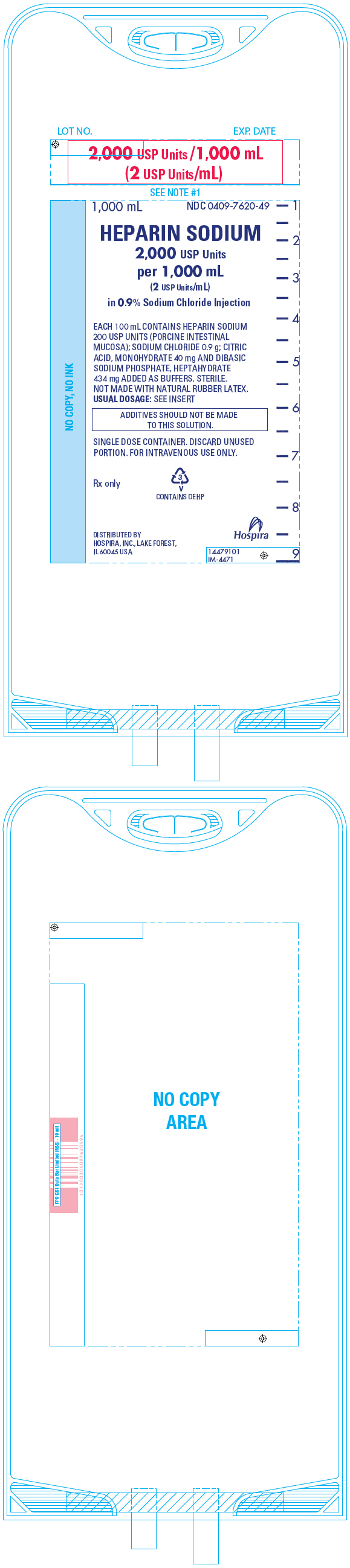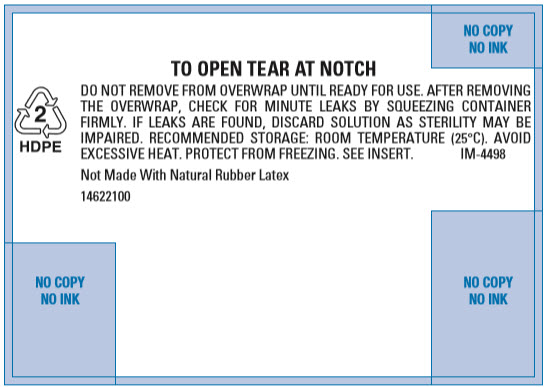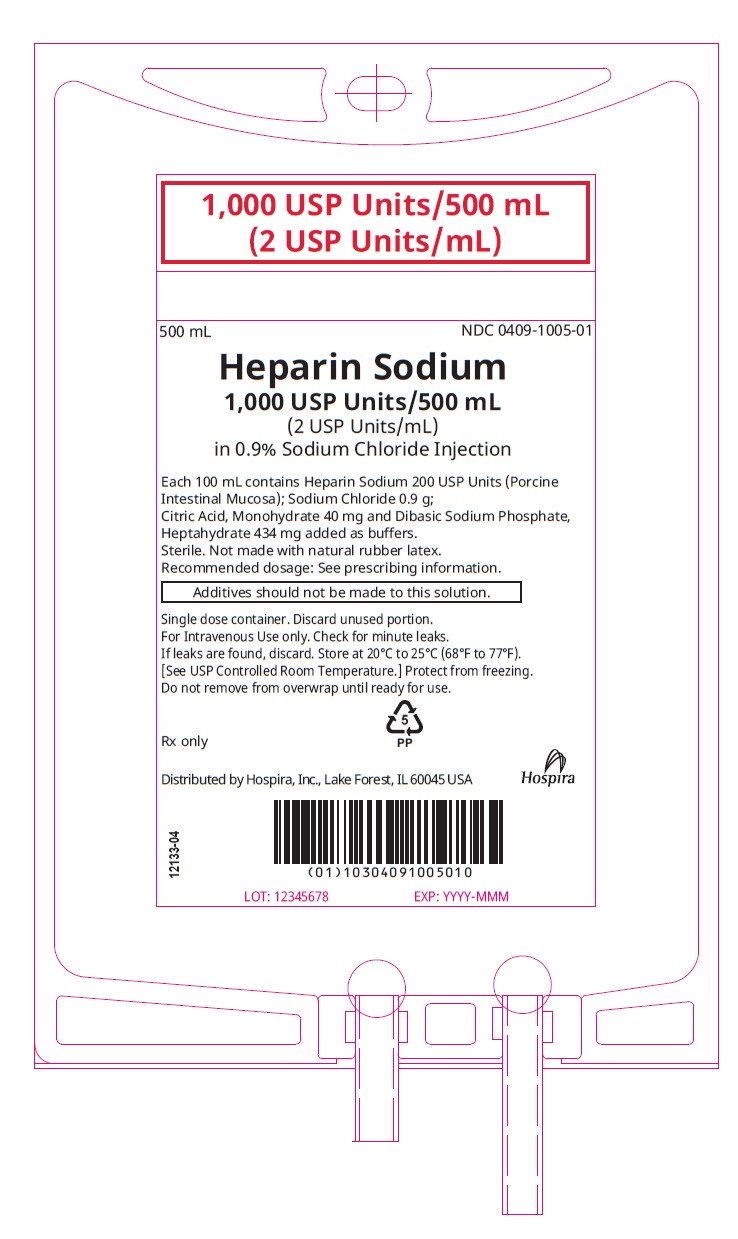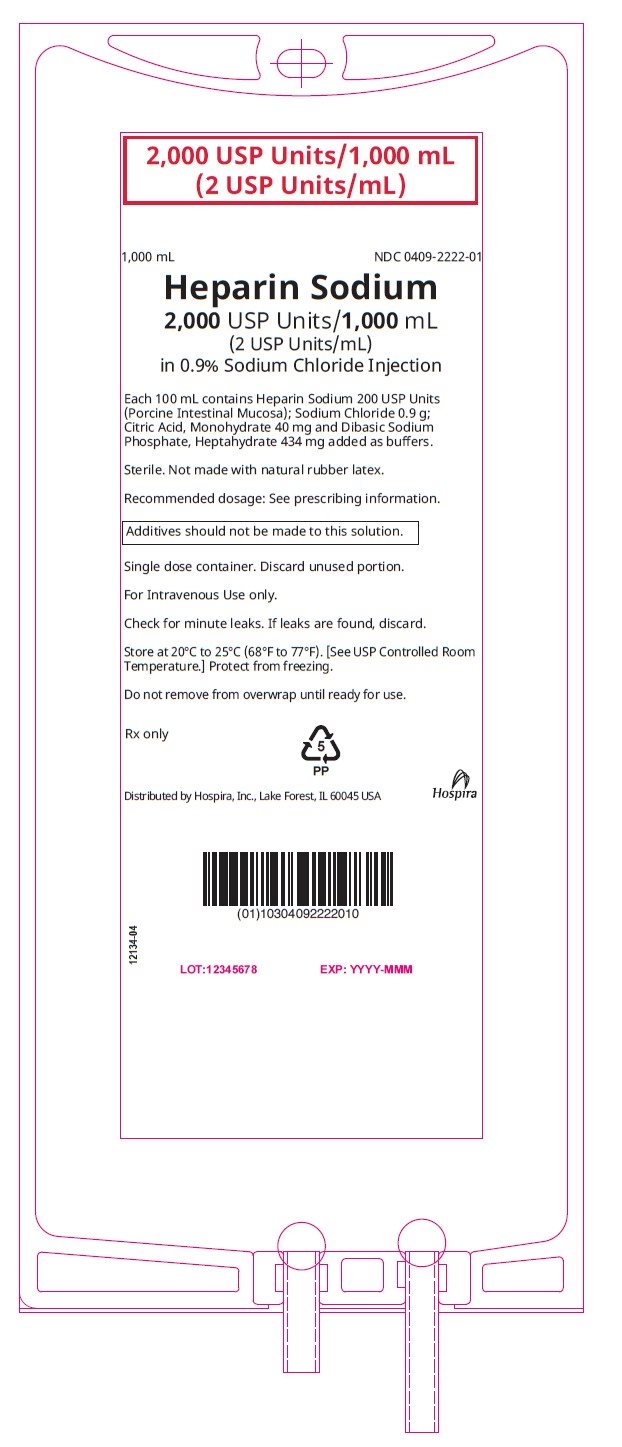 DRUG LABEL: Heparin Sodium
NDC: 0409-7620 | Form: INJECTION, SOLUTION
Manufacturer: Hospira, Inc.
Category: prescription | Type: HUMAN PRESCRIPTION DRUG LABEL
Date: 20251202

ACTIVE INGREDIENTS: HEPARIN SODIUM 200 [USP'U]/100 mL
INACTIVE INGREDIENTS: SODIUM CHLORIDE 0.9 g/100 mL; CITRIC ACID MONOHYDRATE 40 mg/100 mL; SODIUM PHOSPHATE, DIBASIC, HEPTAHYDRATE 434 mg/100 mL; WATER

HIGHLIGHTS OF PRESCRIBING INFORMATION

These highlights do not include all the information needed to use HEPARIN SODIUM IN SODIUM CHLORIDE INJECTION safely and effectively. See full prescribing information for HEPARIN SODIUM IN SODIUM CHLORIDE INJECTION.
HEPARIN SODIUM IN SODIUM CHLORIDE INJECTION, for intravenous use
Initial U.S. Approval: 1939

RECENT MAJOR CHANGES

Warnings and Precautions, Heparin-Induced Thrombocytopenia and Heparin-Induced Thrombocytopenia with Thrombosis (5.2) | 11/2024
Warnings and Precautions, Unresponsiveness to Heparin with Concomitant Use with Andexanet Alfa (5.3) | 11/2025
Warnings and Precautions, Heparin Resistance (5.5) | 11/2024
Warnings and Precautions, Hypersensitivity Reactions (5.6) | 11/2024
Warnings and Precautions, Elevations of Serum Aminotransferases (5.9) | 11/2024

1 INDICATIONS AND USAGE

Heparin Sodium in Sodium Chloride Injection at a concentration of 2 units/mL is indicated as an anticoagulant to maintain catheter patency. (1)

2 DOSAGE AND ADMINISTRATION

Infuse through intravenous catheter at a rate of 6 units per hour. (2.2)

3 DOSAGE FORMS AND STRENGTHS

Heparin Sodium in 0.9% Sodium Chloride Injection is available as: (3)

- Injection: 1,000 USP Units/500 mL (2 USP Units/mL) clear solution in a single-dose flexible plastic container.
- Injection: 2,000 USP Units/1,000 mL (2 USP Units/mL) clear solution in a single-dose flexible plastic container.

4 CONTRAINDICATIONS

Heparin Sodium in Sodium Chloride Injection is contraindicated in patients with the following conditions: (4)

- Uncontrollable active bleeding state, except when this is due to disseminated intravascular coagulation. (5.1)
- History of heparin-induced thrombocytopenia (HIT) and heparin‑induced thrombocytopenia with thrombosis (HITT). (5.2)
- Severe thrombocytopenia. (5.2, 5.4)
- Known hypersensitivity to heparin or pork products. (5.6, 6.1)

5 WARNINGS AND PRECAUTIONS

- Hemorrhage: Fatal hemorrhages have occurred. Monitor for signs of bleeding and manage promptly. (5.1)
- HIT and HITT: Monitor for signs and symptoms and discontinue if indicative of HIT or HITT. (5.2)
- Thrombocytopenia: Monitor platelet count during therapy; discontinue heparin if HIT or HITT is suspected. (5.4)
- Heparin Resistance: Increased resistance to heparin is frequently encountered in fever, thrombosis, thrombophlebitis, infections with thrombosing tendencies, myocardial infarction, cancer and in postsurgical patients. (5.5)
- Hypersensitivity Reactions: Use in patients with prior reactions only in life-threatening situations. (5.6)
- Increased Risk of Bleeding in Older Patients, Especially Women: A higher incidence of bleeding has been reported in patients, particularly women, over 60 years of age. (5.7)
- Hyperkalemia: Measure blood potassium in patients at risk of hyperkalemia before starting heparin therapy and periodically in all patients. (5.8)
- Elevations of Serum Aminotransferases: Interpret elevation of these enzymes with caution. (5.9)
- Laboratory Tests: Periodic platelet counts, hematocrits, and tests for occult blood in stool are recommended during the entire course of heparin therapy, regardless of the route of administration. (5.10)

6 ADVERSE REACTIONS

Most common adverse reactions are: hemorrhage, thrombocytopenia, HIT and HITT, hypersensitivity reactions, heparin resistance, hyperkalemia, and elevations of aminotransferase levels. (6)
To report SUSPECTED ADVERSE REACTIONS, contact Pfizer Inc. at 1-800-438-1985 or FDA at 1-800-FDA-1088 or www.fda.gov/medwatch.

7 DRUG INTERACTIONS

- Drugs that interfere with platelet aggregation or drugs that counteract coagulation may induce bleeding. (7)
- Andexanet alfa may reduce the efficacy of heparin when used concomitantly. (7.3)

8 USE IN SPECIFIC POPULATIONS

Geriatric Use: A higher incidence of bleeding has been reported in patients over 60 years of age, especially women. (5.7, 8.5)

FULL PRESCRIBING INFORMATION

1 INDICATIONS AND USAGE

Heparin Sodium in Sodium Chloride Injection at a concentration of 2 units/mL is indicated as an anticoagulant to maintain catheter patency.

2 DOSAGE AND ADMINISTRATION

2.1 Preparation for Administration

Do not administer unless solution is clear and seal is intact. Parenteral drug products should be inspected visually for particulate matter and discoloration prior to administration, whenever solution and container permit.

Warning: Do not use plastic containers in series connection. Such use could result in air embolism due to residual air being drawn from the primary container before administration of the fluid from the secondary container is completed.

Do not use Heparin Sodium in Sodium Chloride Injection as a “catheter lock flush” product.

Do not admix with other drugs. Discard unused portion.

To Open

Tear outer wrap and remove solution container.

Preparation for Administration

(Use aseptic technique)

1. Close flow control clamp of administration set.
2. Remove cover from outlet port at bottom of container.
3. Insert piercing pin of administration set into port with a twisting motion until the set is firmly seated.
  NOTE: When using a vented administration set, replace bacterial retentive air filter with piercing pin cover. Insert piercing pin with twisting motion until shoulder of air filter housing rests against the outlet port flange.
4. Suspend container from hanger.
5. Squeeze and release drip chamber to establish proper fluid level in chamber.
6. Attach venipuncture device to set.
7. Open clamp to expel air from set and venipuncture device. Close clamp.
8. Perform venipuncture.
9. Regulate rate of administration with flow control clamp.

2.2 Recommended Dosage for Maintenance of Catheter Patency

The recommended starting dose is 6 units per hour by intravenous infusion through an intravenous catheter to maintain catheter patency.

3 DOSAGE FORMS AND STRENGTHS

Heparin Sodium in 0.9% Sodium Chloride Injection is available as:

- Injection: 1,000 USP Units/500 mL (2 USP Units/mL) clear solution in a single-dose flexible plastic container
- Injection: 2,000 USP Units/1,000 mL (2 USP Units/mL) clear solution in a single-dose flexible plastic container

4 CONTRAINDICATIONS

The use of Heparin Sodium in Sodium Chloride Injection is contraindicated in patients with the following conditions:

- Uncontrollable active bleeding state, except when this is due to disseminated intravascular coagulation [see Warnings and Precautions (5.1)]
- History of heparin-induced thrombocytopenia (HIT) and heparin-induced thrombocytopenia with thrombosis (HITT) [see Warnings and Precautions (5.2)]
- Severe thrombocytopenia [see Warnings and Precautions (5.2, 5.4)]
- Known hypersensitivity to heparin or pork products (e.g., anaphylactoid reactions) [see Warnings and Precautions (5.6), Adverse Reactions (6.1)]

5 WARNINGS AND PRECAUTIONS

5.1 Hemorrhage

Avoid using heparin in the presence of major bleeding, except when the benefits of heparin therapy outweigh the potential risks.

Hemorrhage can occur at virtually any site in patients receiving heparin. Fatal hemorrhages have occurred. An unexplained fall in hematocrit or fall in blood pressure, or any other unexplained symptom should lead to serious consideration of a hemorrhagic event.

Use heparin sodium with caution in disease states in which there is increased risk of hemorrhage, including:

- Cardiovascular — Subacute bacterial endocarditis. Severe hypertension.
- Surgical — During and immediately following (a) spinal tap or spinal anesthesia or (b) major surgery, especially involving the brain, spinal cord or eye.
- Hematologic — Conditions associated with increased bleeding tendencies, such as hemophilia, thrombocytopenia and some vascular purpuras.
- Gastrointestinal — Ulcerative lesions and continuous tube drainage of the stomach or small intestine.
- Patients with hereditary antithrombin III deficiency receiving concurrent antithrombin III therapy – The anticoagulant effect of heparin is enhanced by concurrent treatment with antithrombin III (human) in patients with hereditary antithrombin III deficiency. To reduce the risk of bleeding, reduce the heparin dose during concomitant treatment with antithrombin III (human).
- Other — Menstruation, liver disease with impaired hemostasis.

5.2 Heparin-Induced Thrombocytopenia and Heparin-Induced Thrombocytopenia With Thrombosis

Heparin-induced thrombocytopenia (HIT) is a serious immune-mediated reaction. HIT occurs in patients treated with heparin and is due to the development of antibodies to a platelet Factor-4-heparin complex that induce in vivo platelet aggregation. HIT may progress to the development of venous and arterial thromboses, a condition referred to as heparin-induced thrombocytopenia with thrombosis (HITT). Thrombotic events may also be the initial presentation for HITT. These serious thromboembolic events include deep vein thrombosis, pulmonary embolism, cerebral vein thrombosis, limb ischemia, stroke, myocardial infarction, mesenteric thrombosis, thrombus formation on a prosthetic cardiac valve, renal arterial thrombosis, skin necrosis, gangrene of the extremities that may lead to amputation, and possibly death.

Once HIT or HITT is diagnosed or strongly suspected, discontinue all heparin sources (including heparin flushes) and use an alternative anticoagulant.

Immune-mediated HIT is diagnosed based on clinical findings supplemented by laboratory tests confirming the presence of antibodies to heparin, or platelet activation induced by heparin. Obtain platelet counts at baseline and periodically during heparin administration. A drop in platelet count greater than 50% from baseline is considered indicative of HIT. Platelet counts begin to fall 5 to 10 days after exposure to heparin in heparin–naive individuals and reach a threshold by days 7 to 14. In contrast, “rapid onset” HIT can occur very quickly (within 24 hours following heparin initiation), especially in patients with a recent exposure to heparin (i.e., previous 3 months).

Thrombosis development shortly after documenting thrombocytopenia is a characteristic finding in almost half of all patients with HIT.

If the platelet count falls below 100,000/mm^3 or if recurrent thrombosis develops, promptly discontinue heparin, evaluate for HIT and HITT, and, if necessary, administer an alternative anticoagulant. HIT or HITT can occur up to several weeks after the discontinuation of heparin therapy. Patients presenting with thrombocytopenia or thrombosis after discontinuation of heparin sodium should be evaluated for HIT or HITT.

5.3 Unresponsiveness to Heparin with Concomitant Use With Andexanet Alfa

Unresponsiveness to unfractionated heparin leading to non-prolongation of activated clotting times and serious thrombotic events has occurred when unfractionated heparin was administered after use of andexanet alfa for the reversal of direct Factor Xa inhibitors (apixaban and rivaroxaban). Avoid use of heparin after use of andexanet alfa. Use an alternative anticoagulant to heparin [see Drug Interactions (7.3)].

5.4 Thrombocytopenia

Thrombocytopenia in patients receiving heparin has been reported at frequencies up to 30%. It can occur 2 to 20 days (average 5 to 9) following the onset of heparin therapy. Obtain platelet counts before and periodically during heparin therapy. If the count falls below 100,000/mm^3 or if recurrent thrombosis develops, promptly discontinue heparin, evaluate for HIT and HITT, and, if necessary, administer an alternative anticoagulant [see Warnings and Precautions (5.2)].

5.5 Heparin Resistance

Increased resistance to heparin is frequently encountered in fever, thrombosis, thrombophlebitis, infections with thrombosing tendencies, myocardial infarction, cancer, in postsurgical patients, and patients with antithrombin deficiency. Consider measurement of antithrombin levels if heparin resistance is suspected. Monitor coagulation tests frequently in such patients. It may be necessary to adjust the dose of heparin based on coagulation test monitoring, such as anti-Factor Xa levels and/or partial thromboplastin time.

5.6 Hypersensitivity Reactions

Hypersensitivity reactions with chills, fever, and urticaria as the most usual manifestations and also asthma, rhinitis, lacrimation, and anaphylactoid reactions have been reported. Patients with documented hypersensitivity to heparin should be given the drug only in clearly life-threatening situations. Because Heparin Sodium in Sodium Chloride Injection is derived from animal tissue, it should be used with caution in patients with a history of allergy to pork products.

5.7 Increased Risk of Bleeding in Older Patients, Especially Women

A higher incidence of bleeding has been reported in patients, particularly women, over 60 years of age [see Use in Specific Populations (8.5)].

5.8 Hyperkalemia

Heparin can suppress adrenal secretion of aldosterone leading to hyperkalemia, particularly in patients with diabetes mellitus, chronic renal failure, pre-existing metabolic acidosis, a raised plasma potassium, or taking potassium sparing drugs. The risk of hyperkalemia appears to increase with duration of therapy but is usually reversible upon discontinuation of heparin.

Measure blood potassium in patients at risk of hyperkalemia before starting heparin therapy and periodically in all patients treated for more than 5 days or earlier as deemed fit by the clinician.

5.9 Elevations of Serum Aminotransferases

Significant elevations of aspartate aminotransferase (AST) and alanine aminotransferase (ALT) levels have occurred in patients who have received heparin. Elevation of these enzymes in patients receiving heparin should be interpreted with caution. These elevations typically resolve upon heparin discontinuation.

5.10 Laboratory Tests

Periodic platelet counts, hematocrits, and tests for occult blood in stool are recommended during the entire course of heparin therapy, regardless of the route of administration.

6 ADVERSE REACTIONS

The following clinically significant adverse reactions are described elsewhere in the labeling:

- Hemorrhage [see Warnings and Precautions (5.1)]
- Heparin-Induced Thrombocytopenia and Heparin-Induced Thrombocytopenia with Thrombosis [see Warnings and Precautions (5.2)]
- Thrombocytopenia [see Warnings and Precautions (5.4)]
- Heparin Resistance [see Warnings and Precautions (5.5)]
- Hypersensitivity Reactions [see Warnings and Precautions (5.6)]
- Increased Risk of Bleeding in Older Patients, Especially Women [see Warnings and Precautions (5.7)]
- Hyperkalemia [see Warnings and Precautions (5.8)]
- Elevations of Serum Aminotransferases [see Warnings and Precautions (5.9)]

6.1 Postmarketing Experience

The following adverse reactions have been identified during postapproval use of heparin sodium. Because these reactions are reported voluntarily from a population of uncertain size, it is not always possible to reliably estimate their frequency or establish a causal relationship to drug exposure.

Hemorrhage – Hemorrhage is the chief complication that may result from heparin therapy [see Warnings and Precautions (5.1)]. An overly prolonged clotting time or minor bleeding during therapy can usually be controlled by withdrawing the drug [see Overdosage (10)]. Gastrointestinal or urinary tract bleeding during anticoagulant therapy may indicate the presence of an underlying occult lesion. Bleeding can occur at any site but certain specific hemorrhagic complications may be difficult to detect:

- Adrenal hemorrhage, with resultant acute adrenal insufficiency, has occurred during anticoagulant therapy, including fatal cases.
- Ovarian (corpus luteum) hemorrhage developed in a number of women of reproductive age receiving short- or long-term anticoagulant therapy.
- Retroperitoneal hemorrhage.
  Vascular disorders – Contusion, vasospastic reactions (including episodes of painful, ischemic, and cyanosed limbs).

HIT and HITT, including delayed onset [see Warnings and Precautions (5.2)]

Histamine-like reactions – Such reactions have been observed at the site of injections. Necrosis of the skin has been reported at the site of subcutaneous injection of heparin, occasionally requiring skin grafting.

Hypersensitivity – Generalized hypersensitivity reactions have been reported with chills, fever, and urticaria as the most usual manifestations, and asthma, rhinitis, lacrimation, headache, nausea and vomiting, and anaphylactoid reactions, including shock, occurring more rarely. Itching and burning, especially on the plantar site of the feet, may occur [see Warnings and Precautions (5.6)].

Musculoskeletal, connective tissue and bone disorders – Osteoporosis with long-term administration of heparin.

Metabolism and nutrition disorders – Hyperkalemia.

General disorders and administration site conditions – Erythema, mild pain, ulceration.

Elevations of serum aminotransferases – Significant elevations of aspartate aminotransferase (AST) and alanine aminotransferase (ALT) levels have occurred in patients who have received heparin.

Others – Cutaneous necrosis after systemic administration, delayed transient alopecia, priapism, and rebound hyperlipemia on discontinuation of heparin sodium have also been reported.

7 DRUG INTERACTIONS

7.1 Oral Anticoagulants

Heparin sodium may prolong the one-stage prothrombin time. Therefore, when heparin sodium is given with dicumarol or warfarin sodium, a period of at least 5 hours after the last intravenous dose or 24 hours after the last subcutaneous dose should elapse before blood is drawn if a valid prothrombin time is to be obtained.

7.2 Platelet Inhibitors

Drugs such as NSAIDS (including acetylsalicylic acid, ibuprofen, indomethacin, and celecoxib), dextran, phenylbutazone, thienopyridines, dipyridamole, hydroxychloroquine, glycoprotein IIv/IIa antagonists (including abciximab, eptifobatide, and tirofiban), and others that interfere with platelet-aggregation reactions (the main hemostatic defense of heparinized patients) may induce bleeding and should be used with caution in patients receiving heparin sodium. To reduce the risk of bleeding, a reduction in the dose of the antiplatelet agent or heparin is recommended.

7.3 Unresponsiveness to Heparin with Concomitant Use With Andexanet Alfa

Andexanet binds to heparin-bound antithrombin III (ATIII) and may reduce the anticoagulant effect of heparin. Unresponsiveness to unfractionated heparin may lead to serious and life-threatening thrombotic events. Use of andexanet alfa as an antidote for heparin has not been established. Avoid use of heparin after use of andexanet alfa for the reversal of direct Factor Xa inhibitors (apixaban and rivaroxaban). If anticoagulation is needed, use an alternative anticoagulant to heparin [see Warnings and Precautions (5.3)].

7.4 Other Medications that May Interfere With Heparin

Digitalis, tetracyclines, nicotine or antihistamines may partially counteract the anticoagulant action of heparin sodium. Intravenous nitroglycerin administered to heparinized patients may result in a decrease of the partial thromboplastin time with subsequent rebound effect upon discontinuation of nitroglycerin. Careful monitoring of partial thromboplastin time and adjustment of heparin dosage are recommended during coadministration of heparin and intravenous nitroglycerin.

Antithrombin III (human) – The anticoagulant effect of heparin is enhanced by concurrent treatment with antithrombin III (human) in patients with hereditary antithrombin III deficiency. To reduce the risk of bleeding, a reduced dosage of heparin is recommended during treatment with antithrombin III (human).

8 USE IN SPECIFIC POPULATIONS

8.1 Pregnancy

Risk Summary

There are no available data on Heparin Sodium in Sodium Chloride Injection use in pregnant women to inform a drug-associated risk of major birth defects and miscarriage. In published reports, heparin exposure during pregnancy did not show evidence of an increased risk of adverse maternal or fetal outcomes in humans (see Data). Consider the benefits and risks of Heparin Sodium in Sodium Chloride Injection for the mother and possible risks to the fetus when prescribing Heparin Sodium in Sodium Chloride Injection.

The estimated background risk of major birth defects and miscarriage for the indicated population is unknown. All pregnancies have a background risk of birth defect, loss, or other adverse outcomes. In the U.S. general population, the estimated background risk of major birth defects and miscarriage in clinically recognized pregnancies is 2–4% and 15–20%, respectively.

Data

Human Data

The maternal and fetal outcomes associated with uses of heparin via various dosing methods and administration routes during pregnancy have been investigated in numerous studies. These studies generally reported normal deliveries with no maternal or fetal bleeding and no other complications.

Animal Data

In a published study conducted in rats and rabbits, pregnant animals received heparin intravenously during organogenesis at a dose of 10,000 USP Units/kg/day, approximately >50 times the human daily dose. The number of early resorptions increased in both species. There was no evidence of teratogenic effects.

8.2 Lactation

Risk Summary

There is no information regarding the presence of heparin in human milk, the effects on the breastfed child, or the effects on milk production. Due to its large molecular weight, heparin is not likely to be excreted in human milk.

The developmental and health benefits of breastfeeding should be considered along with the mother's clinical need for Heparin Sodium in Sodium Chloride Injection and any potential adverse effects on the breastfed child from Heparin Sodium in Sodium Chloride Injection or from the underlying maternal condition [see Use in Specific Populations (8.4)].

8.4 Pediatric Use

Safety and effectiveness in pediatric patients have not been established.

8.5 Geriatric Use

A higher incidence of bleeding has been reported in patients over 60 years of age, especially women [see Warnings and Precautions (5.7)].

10 OVERDOSAGE

An overdose requires immediate medical attention and treatment.

Symptoms

Bleeding is the chief sign of heparin overdosage. Easy bruising, petechial formations, nosebleeds, blood in urine or tarry stools may be the first signs or symptoms of a heparin overdose. In the event of symptomatic heparin overdose, consider stopping heparin infusion.

Treatment

Neutralization of heparin effect:

When clinical circumstances (bleeding) require reversal of heparinization, protamine sulfate (1% solution) by slow infusion will neutralize heparin sodium. No more than 50 mg should be administered, very slowly, in any 10-minute period. Each mg of protamine sulfate neutralizes approximately 100 USP Heparin units. The amount of protamine required decreases over time as heparin is metabolized. Although the metabolism of heparin is complex, it may, for the purpose of choosing a protamine dose, be assumed to have a half-life of about 30 minutes after intravenous injection.

Ideally, the dose required to neutralize the action of heparin should be guided by blood coagulation tests or calculated from a protamine neutralization test.

Because fatal reactions often resembling anaphylaxis have been reported, protamine sulfate should be given only when resuscitation techniques and treatment of anaphylactoid shock are readily available.

For additional information, consult the prescribing information for Protamine Sulfate Injection, USP.

Blood or plasma transfusions may be necessary; these dilute but do not neutralize heparin.

Consider contacting the Poison Help line (1-800-222-1222) or a medical toxicologist for additional overdose management recommendations.

11 DESCRIPTION

Intravenous solutions with heparin sodium (derived from porcine intestinal mucosa) are sterile, nonpyrogenic fluids for intravenous administration. Each 100 mL contains heparin sodium 200 USP Units; sodium chloride, 0.9 g; citric acid, monohydrate, 40 mg and dibasic sodium phosphate, heptahydrate, 434 mg added as buffers. Each liter contains the following electrolytes: Sodium 186.4 mEq; phosphate (as HPO4=) 32.4 mEq, citrate 5.7 mEq and chloride 154 mEq. Osmolar concentration, 378 mOsmol/liter (calc.); pH 7.0 (5.0 – 7.5).

Heparin Sodium, USP is a heterogeneous group of straight-chain anionic mucopolysaccharides, called glycosaminoglycans having anticoagulant properties. Although others may be present, the main sugars occurring in heparin are: (1) α-L-iduronic acid 2-sulfate, (2) 2-deoxy-2-sulfamino-α-D-glucose-6-sulfate, (3) β-D-glucuronic acid, (4) 2-acetamido-2-deoxy-α-D-glucose, and (5) α-L-iduronic acid. These sugars are present in decreasing amounts, usually in the order (2) > (1) > (4) > (3) > (5), and are joined by glycosidic linkages, forming polymers of varying sizes. Heparin is strongly acidic because of its content of covalently linked sulfate and carboxylic acid groups. In heparin sodium, the acidic protons of the sulfate units are partially replaced by sodium ions. The potency is determined by a biological assay using a USP reference standard based on units of heparin activity per milligram.

Structure of Heparin Sodium (representative subunits):

Sodium Chloride, USP is chemically designated NaCl, a white crystalline compound freely soluble in water.

Dibasic Sodium Phosphate, USP (heptahydrate), is chemically designated (Na2HPO4 ∙ 7H2O), colorless or white granular salt freely soluble in water.

Citric Acid, USP, hydrous (monohydrate) is chemically designated C6H8O7 ∙ H2O, colorless, translucent crystals or white crystalline powder very soluble in water. It has the following structural formula:

Water for Injection, USP is chemically designated H2O.

The flexible plastic container is fabricated from either polyvinylchloride or polyolefin plastic. Water can permeate from inside the container into the overwrap but not in amounts sufficient to affect the solution significantly. Solutions inside the plastic container also can leach out certain of its chemical components in very small amounts before the expiration period is attained. However, the safety of the plastic has been confirmed by tests in animals according to USP biological standards for plastic containers.

12 CLINICAL PHARMACOLOGY

12.1 Mechanism of Action

Heparin interacts with the naturally occurring plasma protein, antithrombin III, to induce a conformational change, which markedly enhances the serine protease activity of Antithrombin II, thereby inhibiting the activated coagulation factors involved in the closing sequence, particularly Xa and IIa. Small amounts of heparin inhibit Factor Xa, and larger amounts inhibit thrombin (Factor IIa).

Heparin also prevents the formation of a stable fibrin clot by inhibiting the activation of the fibrin stabilizing factor. Heparin does not have fibrinolytic activity; therefore, it will not lyse existing clots.

12.2 Pharmacodynamics

Various times (activated clotting time, activated partial thromboplastin time, prothrombin time, whole blood clotting time) are prolonged by full therapeutic doses of heparin; in most cases, they are not measurably affected by low doses of heparin. Bleeding time is usually unaffected by heparin.

12.3 Pharmacokinetics

Absorption

Heparin is not absorbed through the gastrointestinal tract and therefore administered via parenteral route. Peak plasma concentration and the onset of action are achieved immediately after intravenous administration.

Distribution

Heparin is highly bound to antithrombin, fibrinogens, globulins, serum proteases and lipoproteins. The volume of distribution is 0.07 L/kg.

Elimination

Metabolism

Heparin does not undergo enzymatic degradation.

Excretion

Heparin is mainly cleared from the circulation by liver and reticuloendothelial cells mediated uptake into extravascular space. Heparin undergoes biphasic clearance, a) rapid saturable clearance (zero‑order process due to binding to proteins, endothelial cells and macrophages) and b) slower first order elimination. Low doses of heparin are cleared mostly by a saturable, rapid, zero-order process. Slower first order elimination usually occurs with very high doses of heparin and is dependent on renal function. The plasma half-life is dose-dependent and it ranges from 0.5 to 2 h.

Specific Populations

Geriatric Patients

Patients over 60 years of age, following similar doses of heparin, may have higher plasma levels of heparin and longer activated partial thromboplastin times (APTTs) compared with patients under 60 years of age [see Use in Specific Populations (8.5)].

Patients with Renal and Hepatic Impairment

The rate of clearance of unfractionated heparin may be decreased in patients with renal or hepatic impairment. Patients with renal or hepatic impairment, following similar doses of heparin may have higher plasma levels of heparin compared with patients with normal renal and hepatic function [see Warnings and Precautions (5.1)].

13 NONCLINICAL TOXICOLOGY

13.1 Carcinogenesis, Mutagenesis, Impairment of Fertility

No long‑term studies in animals have been performed to evaluate carcinogenic potential of heparin. Also, no reproduction studies in animals have been performed concerning mutagenesis or impairment of fertility.

16 HOW SUPPLIED/STORAGE AND HANDLING

Heparin Sodium in 0.9% Sodium Chloride Injection is a clear solution and is available in single-dose containers as follows:

Unit of Sale | Concentration
NDC 0409-7620-03; Case of 18 Single-dose flexible plastic containers | 1,000 USP Units/500 mL; (2 USP Units/mL)
NDC 0409-1005-20; Case of 20 Single-dose flexible plastic containers | 1,000 USP Units/500 mL; (2 USP Units/mL)
NDC 0409-7620-59; Case of 12 Single-dose flexible plastic containers | 2,000 USP Units/1,000 mL; (2 USP Units/mL)
NDC 0409-2222-12; Case of 12 Single-dose flexible plastic containers | 2,000 USP Units/1,000 mL; (2 USP Units/mL)

STORAGE AND HANDLING

Store at 20°C to 25°C (68°F to 77°F). [See USP Controlled Room Temperature.] Protect from freezing.

17 PATIENT COUNSELING INFORMATION

Hemorrhage

Inform patients that it may take them longer than usual to stop bleeding, that they may bruise and/or bleed more easily when they are treated with heparin, and that they should report any unusual bleeding or bruising to their physician. Hemorrhage can occur at virtually any site in patients receiving heparin. Fatal hemorrhages have occurred [see Warnings and Precautions (5.1)].

Prior to Surgery

Advise patients to inform physicians and dentists that they are receiving heparin before any surgery is scheduled [see Warnings and Precautions (5.1)].

Heparin-Induced Thrombocytopenia

Inform patients of the risk of heparin-induced thrombocytopenia (HIT). HIT may progress to the development of venous and arterial thromboses, a condition known as heparin-induced thrombocytopenia and thrombosis (HITT). HIT or HITT can occur up to several weeks after the discontinuation of heparin therapy [see Warnings and Precautions (5.2)].

Hypersensitivity

Inform patients that generalized hypersensitivity reactions have been reported. Necrosis of the skin has been reported at the site of subcutaneous injection of heparin [see Warnings and Precautions (5.6), Adverse Reactions (6.1)].

Other Medications

Because of the risk of hemorrhage, advise patients to inform their physicians and dentists of all medications they are taking, including non-prescription medications, and before starting any new medication [see Drug Interactions (7)].

This product’s labeling may have been updated. For the most recent prescribing information, please visit www.pfizer.com.

For medical information about Heparin Sodium in Sodium Chloride Injection, please visit www.pfizermedinfo.com or call 1-800-438‑1985.

Distributed by Hospira, Inc., Lake Forest, IL 60045 USA

LAB-0807-8.0

PRINCIPAL DISPLAY PANEL - 500 mL Bag - 7620

1,000 USP Units/500 mL
(2 USP Units/mL)

500 mL
NDC 0409-7620-13

HEPARIN SODIUM
1,000 USP Units/500 mL
(2 USP Units/mL)
in 0.9% Sodium Chloride Injection

EACH 100 mL CONTAINS HEPARIN SODIUM 200 USP UNITS
(PORCINE INTESTINAL MUCOSA); SODIUM CHLORIDE 0.9 g;
CITRIC ACID, MONOHYDRATE 40 mg AND DIBASIC SODIUM
PHOSPHATE, HEPTAHYDRATE 434 mg ADDED AS BUFFERS.
STERILE. NOT MADE WITH NATURAL RUBBER LATEX.
USUAL DOSAGE: SEE INSERT

ADDITIVES SHOULD NOT BE MADE TO THIS SOLUTION.

SINGLE DOSE CONTAINER. DISCARD UNUSED PORTION. FOR
INTRAVENOUS USE ONLY.

3
V
CONTAINS DEHP

Rx only

DISTRIBUTED BY
HOSPIRA, INC., LAKE FOREST, IL 60045 USA

Hospira

14478901
IM-4470

PRINCIPAL DISPLAY PANEL - 1,000 mL Bag - 7620

LOT NO.
EXP. DATE

2,000 USP Units /1,000 mL
(2 USP Units/mL)

1,000 mL
NDC 0409-7620-49

HEPARIN SODIUM
2,000 USP Units
per 1,000 mL
(2 USP Units/mL)
in 0.9% Sodium Chloride Injection

EACH 100 mL CONTAINS HEPARIN SODIUM
200 USP UNITS (PORCINE INTESTINAL
MUCOSA); SODIUM CHLORIDE 0.9 g; CITRIC
ACID, MONOHYDRATE 40 mg AND DIBASIC
SODIUM PHOSPHATE, HEPTAHYDRATE
434 mg ADDED AS BUFFERS. STERILE.
NOT MADE WITH NATURAL RUBBER LATEX.
USUAL DOSAGE: SEE INSERT

ADDITIVES SHOULD NOT BE MADE
TO THIS SOLUTION.

SINGLE DOSE CONTAINER. DISCARD UNUSED
PORTION. FOR INTRAVENOUS USE ONLY.

Rx only

3
V
CONTAINS DEHP

DISTRIBUTED BY
HOSPIRA, INC., LAKE FOREST,
IL 60045 USA

Hospira

14479101
IM-4471

PRINCIPAL DISPLAY PANEL - Bag Overwrap

TO OPEN TEAR AT NOTCH

2
HDPE

DO NOT REMOVE FROM OVERWRAP UNTIL READY FOR USE. AFTER REMOVING
THE OVERWRAP, CHECK FOR MINUTE LEAKS BY SQUEEZING CONTAINER
FIRMLY. IF LEAKS ARE FOUND, DISCARD SOLUTION AS STERILITY MAY BE
IMPAIRED. RECOMMENDED STORAGE: ROOM TEMPERATURE (25°C). AVOID
EXCESSIVE HEAT. PROTECT FROM FREEZING. SEE INSERT.

IM-4498

Not Made With Natural Rubber Latex

14622100

PRINCIPAL DISPLAY PANEL - 500 mL Bag Label - 1005

500mL
NDC 0409-1005-01

Heparin Sodium
1,000 USP Units / 500 mL
(2 USP Units / mL)
in 0.9% Sodium Chloride Injection

Each 100 mL contains Heparin Sodium 200 USP Units (Porcine
Intestinal Mucosa); Sodium Chloride 0.9 g;
Citric acid, Monohydrate 40 mg and Dibasic Sodium Phosphate,
Heptahydrate 434 mg added as buffers.
Sterile. Not made with natural rubber latex.
Recommended dosage: See prescribing information.
Additives should not be made to this solution.
Single dose container. Discard unused portion.
For Intravenous Use only. Inspect bag by squeezing firmly.
If leaks are found, discard. Store at 20℃ to 25℃ (68℉ to 77℉).
[See USP Controlled Room Temperature.] Protect from freezing.
Do not remove from overwrap until ready for use.

Rx only

5
PP

Distributed by Hospira, Inc., Lake Forest, IL 60045 USA

Hospira

PRINCIPAL DISPLAY PANEL - 1000 mL Bag Label - 2222

2,000 USP Units / 1,000 mL
(2 USP Units / mL)

1,000mL
NDC 0409-2222-01

Heparin Sodium
2,000 USP Units / 1,000 mL
(2 USP Units / mL)
in 0.9% Sodium Chloride Injection

Each 100 mL contains Heparin Sodium 200 USP Units
(Porcine Intestinal Mucosa); Sodium Chloride 0.9 g;
Citric acid, Monohydrate 40 mg and Dibasic Sodium
Phosphate, Heptahydrate 434 mg added as buffers.

Sterile. Not made with natural rubber latex.

Recommended dosage: See prescribing information.

Additives should not be made to this solution.

Single dose container. Discard unused portion.

For Intravenous Use only.

Check for minute leaks. If leaks are found, discard.

Store at 20℃ to 25℃ (68℉ to 77℉). [See USP Controlled Room
Temperature.] Protect from freezing.

Do not remove from overwrap until ready for use.

Rx only

5
PP

Distributed by Hospira, Inc., Lake Forest, IL 60045 USA

Hospira